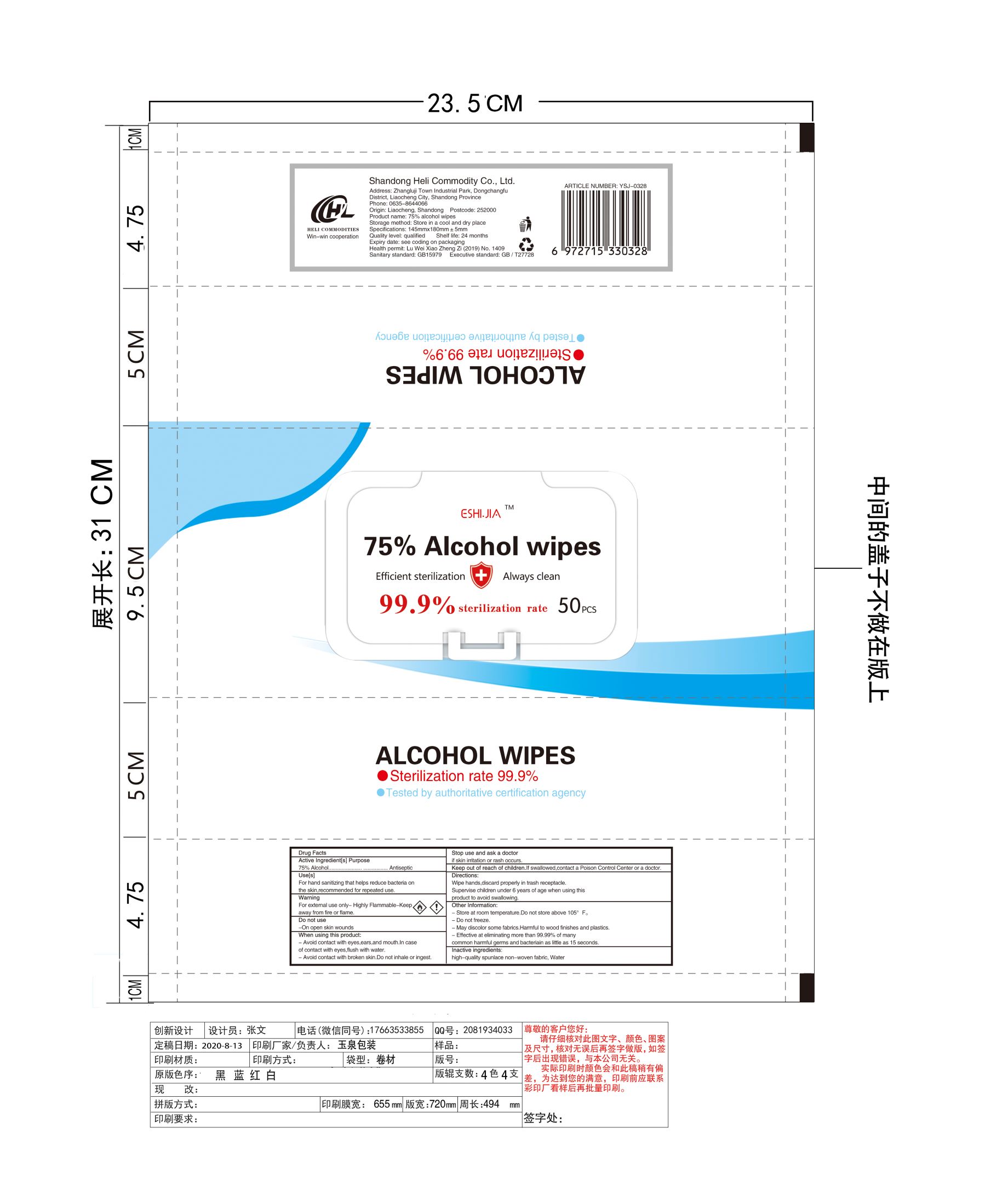 DRUG LABEL: 75% Alcohol Wipes
NDC: 55676-002 | Form: CLOTH
Manufacturer: SHANDONG HELI DAILY NECESSITIES CO.,LTD
Category: otc | Type: HUMAN OTC DRUG LABEL
Date: 20200909

ACTIVE INGREDIENTS: ALCOHOL 75 mL/100 mL
INACTIVE INGREDIENTS: WATER

75% Alcohol Wipes
5pcs NDC: 55676-002-01
10pcs NDC: 55676-002-02
40pcs NDC: 55676-002-03
50pcs NDC: 55676-002-04
80pcs NDC: 55676-002-05

Active Ingredient(s)

75% Alcohol

Purpose

Antiseptic

Use

For hand sanitizing that helps reduce bacteria on the skin, recommended for repeated use.

Warnings

- For external use only.
- Highly Flammable - Keep away from fire or flame.

Do not use

- On open skin wounds.

WHEN USING

- Avoid contact with eyes, ears, and mouth. In case of contact with eyes, flush with water.
- Avoid contact with broken skin. Do not inhale or ingest.

Stop use and ask a doctor if skin irritation or rash occurs.

Keep out of reach of children. If swallowed, contact a Poison Control Center or a doctor.

Directions

- Wipe hands, discard properly in trash receptacle.
- Supervise children under 6 years of age when using this product to avoid swallowing.

Other information

- Store at room temperature. Do not store above 105℉.
- Do not freeze
- May discolor some fabrics. Harmful to wood finishes and plastics.
- Effective at eliminating more than 99.99% of many common harmful germs and bacteriain as little as 15 seconds.

Inactive ingredients

high-quality spunlace non-woven fabric, Water.

Package Label - Principal Display Panel

5pcs NDC: 55676-002-01

10pcs NDC: 55676-002-02

40pcs NDC: 55676-002-03

50pcs NDC: 55676-002-04

80pcs NDC: 55676-002-05